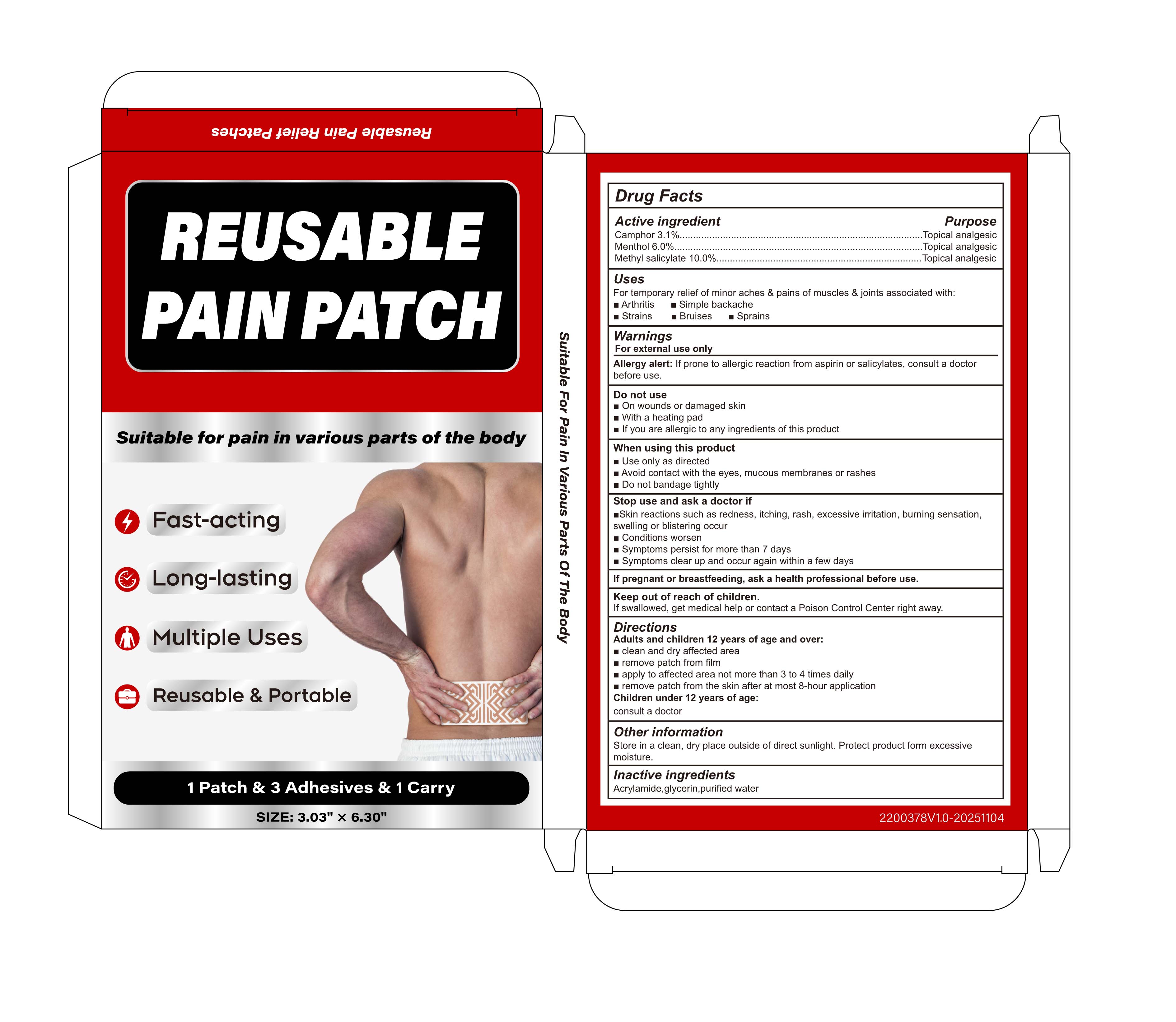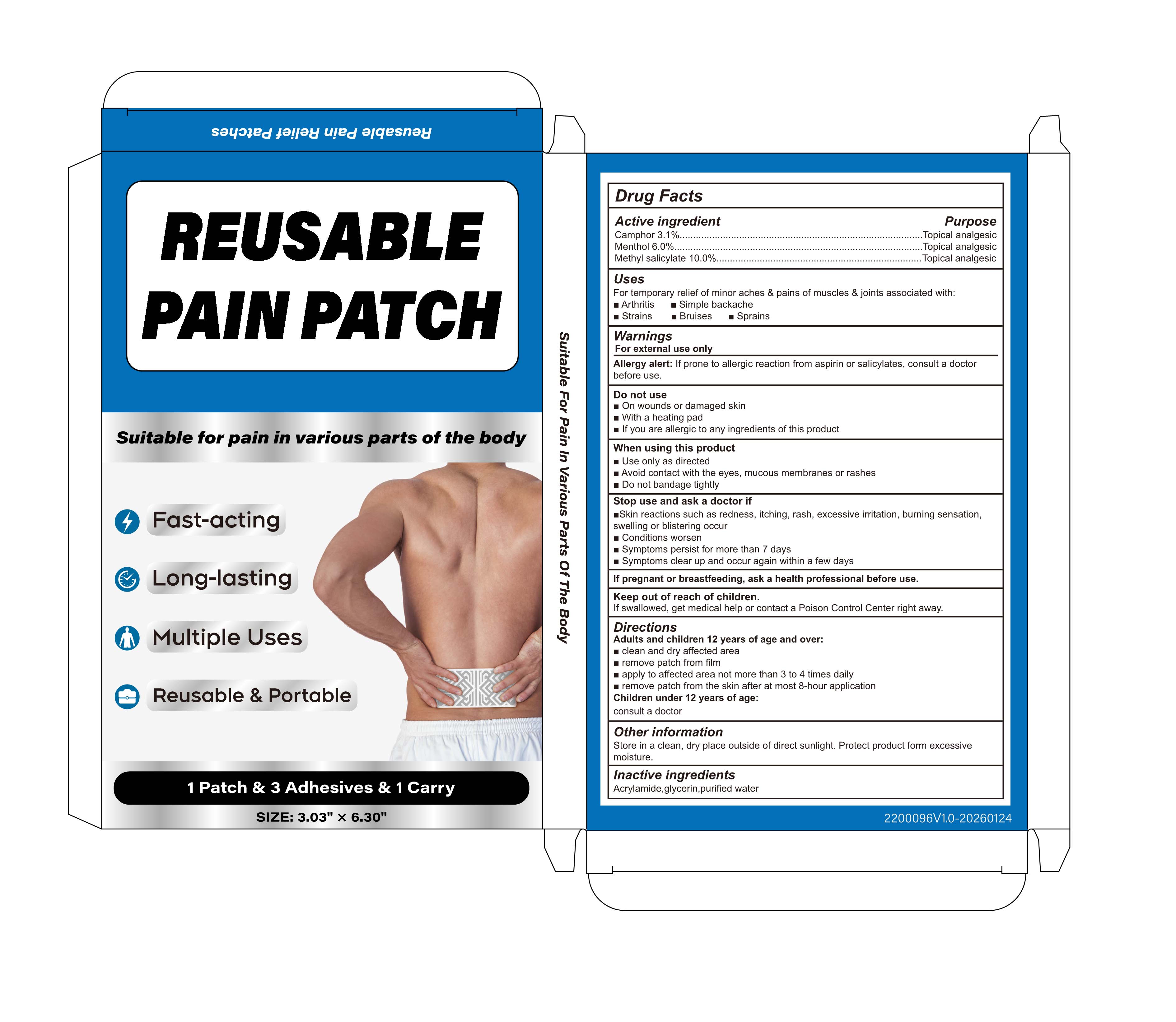 DRUG LABEL: PAIN
NDC: 87255-005 | Form: PATCH
Manufacturer: Shenzhen Mengyue Technology Co., Ltd.
Category: otc | Type: HUMAN OTC DRUG LABEL
Date: 20260127

ACTIVE INGREDIENTS: METHYL SALICYLATE 10 g/100 1; CAMPHOR (NATURAL) 3.1 g/100 1; MENTHOL 6 g/100 1
INACTIVE INGREDIENTS: ACRYLAMIDE; GLYCERIN; WATER

005 PAIN PATCH

ACTIVE INGREDIENT

Camphor 3.1%, Menthol 6.0%, Methyl salicylate 10.0%

PURPOSE

Topical analgesic

Uses

For temporary relief of minor aches & pains of muscles & joints associated with:

- Arthritis

- Simple backache

- Strains

- Bruises

- Sprains

Warnings

For external use only

Allergy alert: If prone to allergic reaction from aspirin or salicylates, consult a doctor before use.

Do not use

- On wounds or damaged skin

- With a heating pad

- If you are allergic to any ingredients of this product

When using this product

- Use only as directed

- Avoid contact with the eyes, mucous membranes or rashes

- Do not bandage tightly

Stop use and ask a doctor if

- Skin reactions such as redness, itching, rash, excessive irritation, burning sensation, swelling or blistering occur

- Conditions worsen

- Symptoms persist for more than 7 days

- Symptoms clear up and occur again within a few days

If pregnant or breastfeeding, ask a health professional before use.

Keep out of reach of children.

If swallowed, get medical help or contact a Poison Control Center right away.

Directions

- Adults and children 12 years of age and over:

- clean and dry affected area remove patch from film

- apply to affected area not more than 3 to 4 times daiy

- remove patch from the skin after at most 8-hour application

Children under 12 years of age:

consult a doctor

Other information

Store in a clean, dry place outside of direct sunlight. Protect product form excessive moisture.

Inactive ingredients

Acrylamide, glycerin, purified water